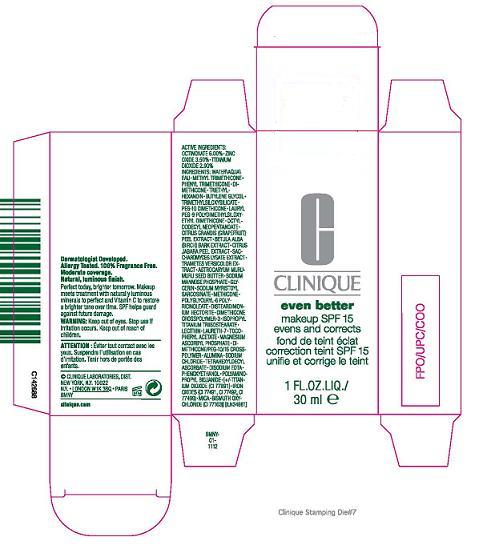 DRUG LABEL: EVEN BETTER MAKEUP
NDC: 49527-712 | Form: LIQUID
Manufacturer: CLINIQUE LABORATORIES INC
Category: otc | Type: HUMAN OTC DRUG LABEL
Date: 20100419

ACTIVE INGREDIENTS: OCTINOXATE 6.0 mL/100 mL; ZINC OXIDE 3.5 mL/100 mL; TITANIUM DIOXIDE 2.9 mL/100 mL

ACTIVE INGREDIENT

ACTIVE INGREDIENTS: OCTINOXATE 6.00% [] ZINC OXIDE 3.50% [] TITANIUM DIOXIDE 2.90%

WARNINGS

WARNING: KEEP OUT OF EYES. STOP USE IF IRRITATION OCCURS. KEEP OUT OF REACH OF CHILDREN.

PACKAGE LABEL

PRINCIPAL DISPLAY PANEL:
CLINIQUE
EVEN BETTER
MAKEUP SPF 15
EVENS AND CORRECTS
1 FL OZ. LIQ./ 30 ML
CLINIQUE LABORATORIES, DIST.
NEW YORK, NY 10022
CLINIQUE.COM